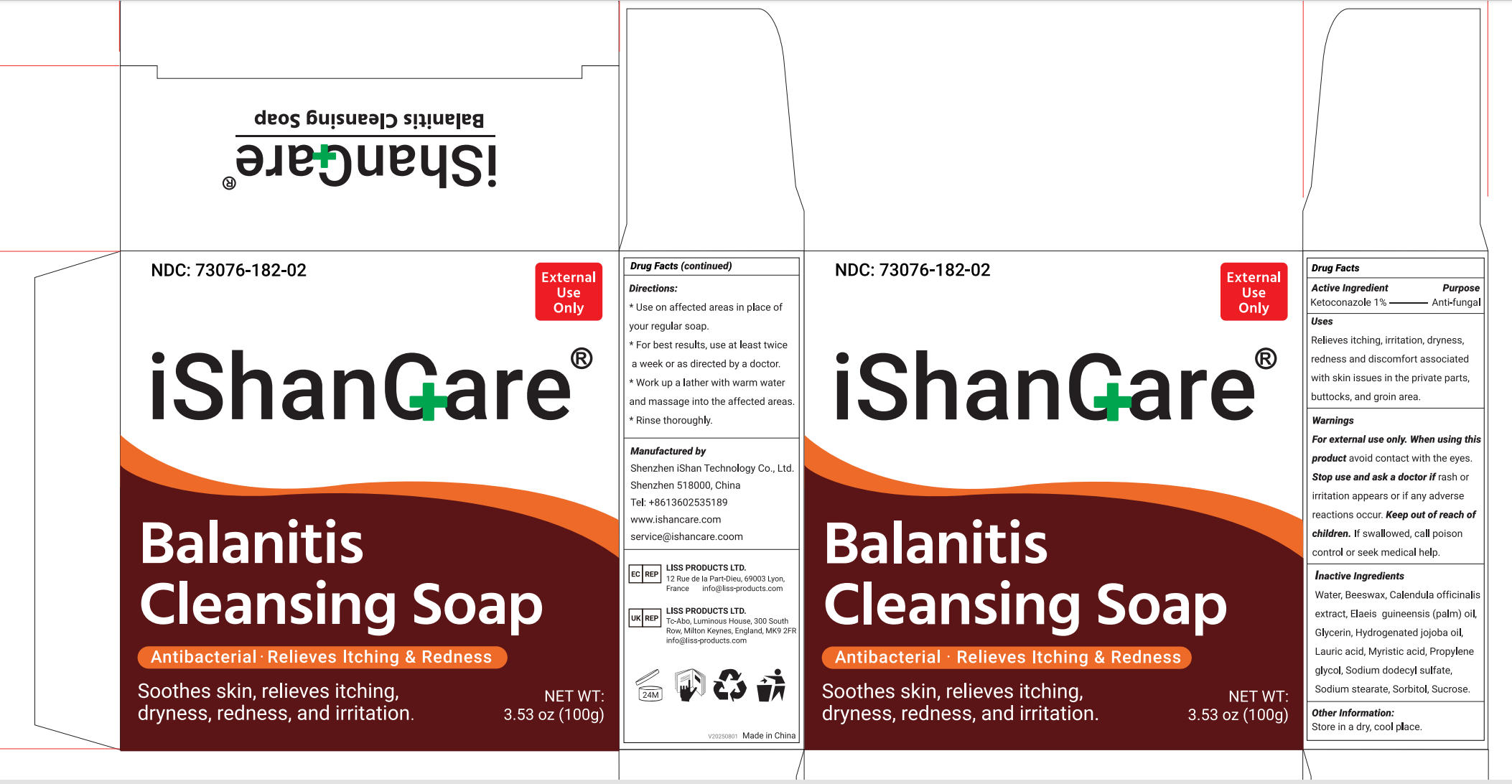 DRUG LABEL: iShanCare Balanitis Cleansing
NDC: 73076-182 | Form: SOAP
Manufacturer: Shenzhen Ishan Technology Co., Ltd
Category: otc | Type: HUMAN OTC DRUG LABEL
Date: 20260212

ACTIVE INGREDIENTS: KETOCONAZOLE 1 g/100 g
INACTIVE INGREDIENTS: ELAEIS GUINEENSIS (PALM) OIL; WATER; CALENDULA OFFICINALIS WHOLE; HYDROGENATED JOJOBA OIL; PROPOLIS WAX; GLYCERIN; BEESWAX; SUCROSE; MYRISTIC ACID; SODIUM STEARATE; SODIUM DODECYLBENZENESULFONATE; LAURIC ACID

Active ingredients

Ketoconazole 1%---------- Anti-fungal

Inactive Ingredients

Water, Beeswax, Calendula officinalisextract, Elaeis guineensis (palm) oiGlycerin, Hydrogenated jojoba oil,Lauric acid, Myristic acid, Propyleneglycol, Sodium dodecyl sulfate,Sodium stearate, Sorbitol, Sucrose.

Uses

Relieves itching, irritation, dryness, redness and discomfort associated with skin issues in the private parts, buttocks, and groin area.

Warnings

For external use only

When using this product

avoid contact with the eyes

Stop use

Stop use and ask a doctor if rash or irritation appears or if any
adverse reactions occur

Ask a doctor

Stop use and ask
a doctor if rash or irritation appears or if any
adverse reactions occur

Keep out of reach of children

If swallowed, call a poison control center or seek medical attention immediately.

Dosage and administration

First, wet your skin. Then lather the soap in
your hands, and apply the lather to your face
or body in a circular motion. Leave on skin for
two minutes, then rinse completely and pat dry
gently.

Other information

Store at room temperature.

INDICATIONS AND USAGE

First, wet your skin. Then lather the soap in your hands, and apply the lather to your face or body in a circular motion. Leave on skin fortwo minutes, then rinse completely and pat dry gently.